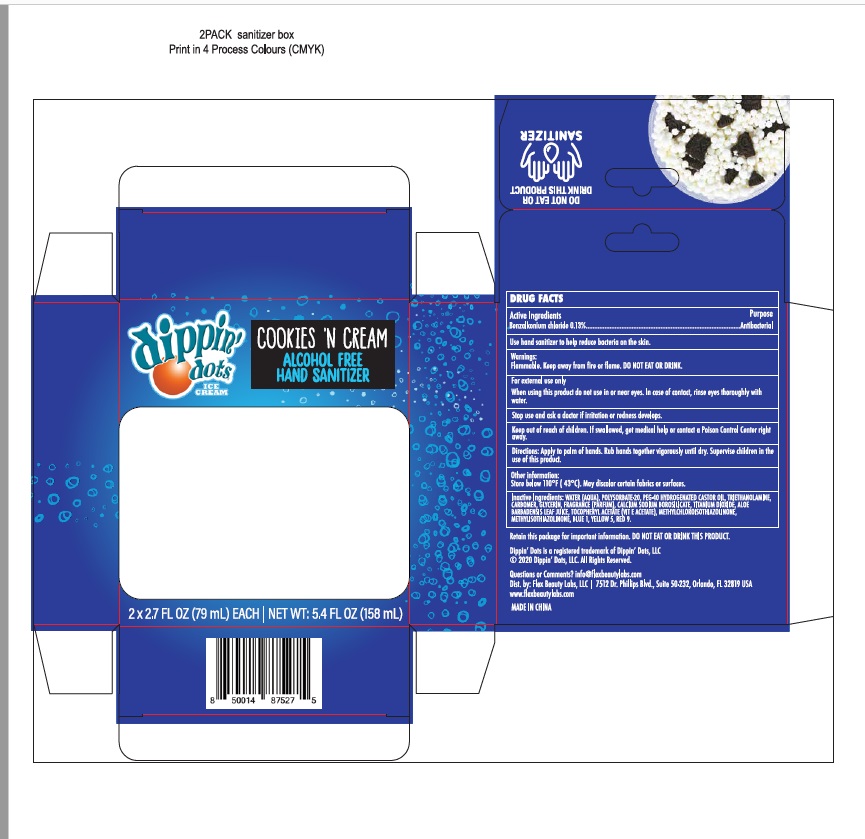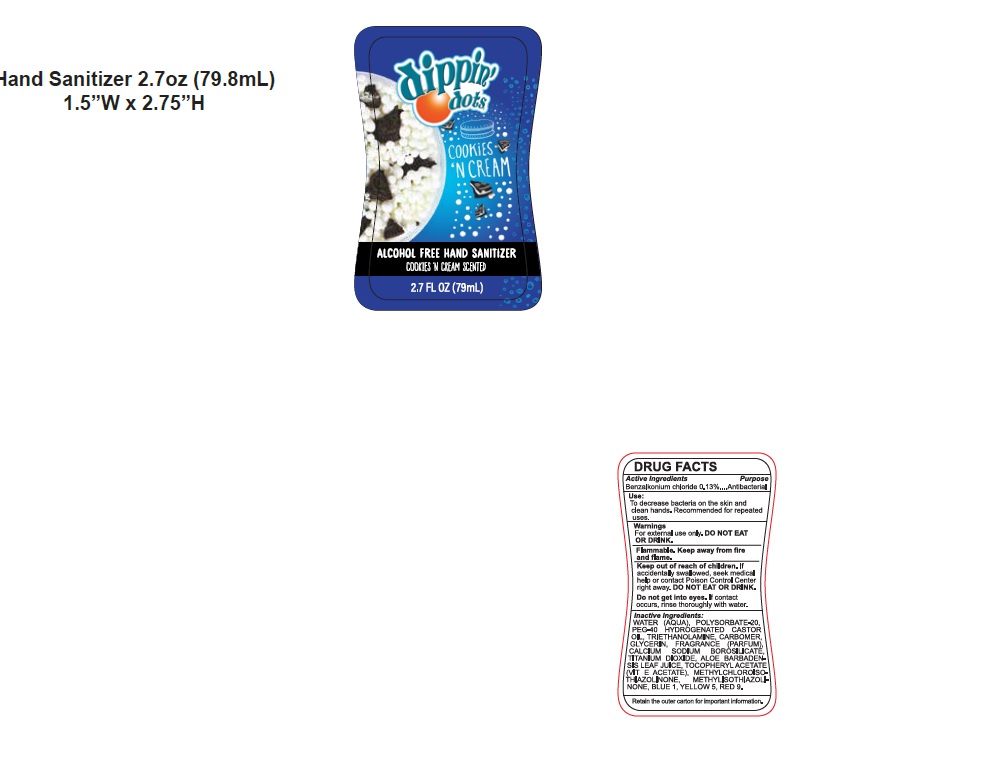 DRUG LABEL: DIPPIN DOTS ALCOHOL FREE HAND SANITIZER
NDC: 72308-026 | Form: GEL
Manufacturer: Flex Beauty Labs
Category: otc | Type: HUMAN OTC DRUG LABEL
Date: 20200804

ACTIVE INGREDIENTS: BENZALKONIUM CHLORIDE 0.13 mg/1 mL
INACTIVE INGREDIENTS: WATER; POLYSORBATE 20; POLYOXYL 40 HYDROGENATED CASTOR OIL; TROLAMINE; CARBOMER HOMOPOLYMER, UNSPECIFIED TYPE; PROPYLENE GLYCOL; GLYCERIN; TITANIUM DIOXIDE; ALOE VERA LEAF; .ALPHA.-TOCOPHEROL ACETATE; METHYLCHLOROISOTHIAZOLINONE; METHYLISOTHIAZOLINONE; FD&C BLUE NO. 1; FD&C YELLOW NO. 5

DIPPIN DOTS ALCOHOL FREE HAND SANITIZER

Active Ingredients

Benzalkonium Chloride 0.13%.........Antibacterial

Purpose

Antibacterial

Use

To decrease bacteria on the skin and clean hands.

Recommended for repeated uses.

Safety Instructions

For extemal use only.

Do not Eat Or Drink

Flammable.Keep away from fire and flame.

When using this product

In case of contact,rinse eyes thoroughly with water.

Do not use in or near eyes.

KEEP OUT OF REACH OF CHILDREN

If accidentally swallowed, seek medical help or contact Poison Control center right away.

Inactive Ingredients

Water (aqua), Polysorbate-20, PEG-40 Hydrogenated,Triethanolamine, Carbomer, Fragrance, Glycerin. Propylene Glycol, Calcium Sodium Borosilicate , Titanium Dioxide , Aloe Barbdensis Leaf Juice,Tocopheryl Acetate, Methylchloroisothiazolinone,Methylsothiazolinone ,Blue 1

Yellow 5,Red 9.

Directions

- apply palmful to hands.
- rub hands together vigorously until dry.
- supervise children in the use of this product.